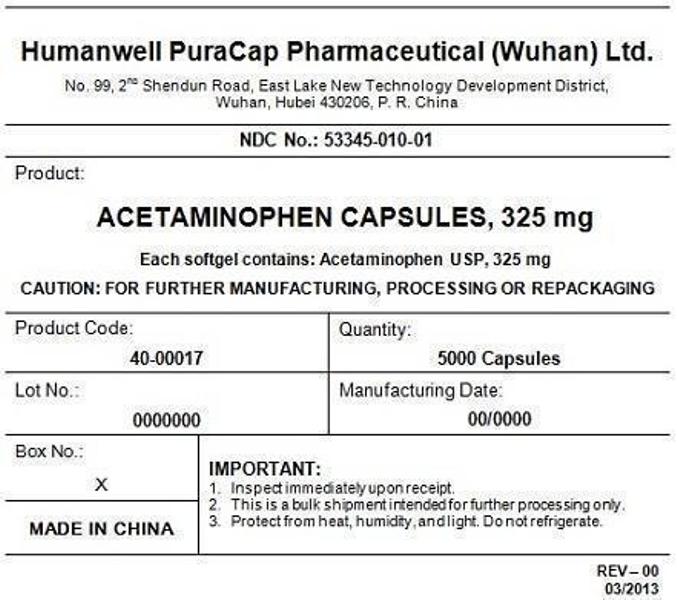 DRUG LABEL: ACETAMINOPHEN (RED)
NDC: 53345-010 | Form: CAPSULE, LIQUID FILLED
Manufacturer: Humanwell PuraCap Pharmaceutical (Wuhan), Ltd.
Category: otc | Type: HUMAN OTC DRUG LABEL
Date: 20241125

ACTIVE INGREDIENTS: ACETAMINOPHEN 325 mg/1 1
INACTIVE INGREDIENTS: FD&C RED NO. 40; FD&C YELLOW NO. 6; GELATIN; GLYCERIN; POLYETHYLENE GLYCOL, UNSPECIFIED; POVIDONE; PROPYLENE GLYCOL; WATER; SORBITOL

ACETAMINOPHEN CAPSULES 325 mg, liquid filled

Drug Facts

Active ingredient (in each capsule)

Acetaminophen 325 mg

Purpose

Pain reliever/ fever reducer

Uses

- Temporarily relieves minor aches and pains due to :
  - headache
  - muscular aches
  - backache
  - minor pain of arthritis
  - the common cold
  - toothache
  - premenstrual and menstrual cramps
- temporarily reduces fever

Warnings

Liver warning:This product contains acetaminophen. The maximum daily dose of this product is 10 softgels (3,250 mg) in 24 hours for adults or 5 softgels (1,625 mg) in 24 hours for children. Severe liver damage may occur if

- adult takes more than 4,000 mg of acetaminophen in 24 hours
- child takes more than 5 doses in 24 hours, which is the maximum daily amount
- taken with other drugs containing acetaminophen
- adult has 3 or more alcoholic drinks every day while using this product

Do not use

- with any other drug containing acetaminophen (prescription or nonprescription). If you are not sure whether a drug contains acetaminophen, ask a doctor or pharmacist
- if you are allergic to acetaminophen or any of the inactive ingredients in this product

Ask a doctor before use if the user hasliver disease

Ask a doctor or pharmacist before use if the user istaking the blood thinning drug warfarin

Stop use and ask a doctor if

- pain gets worse or lasts more than 10 days in adults
- pain gets worse or lasts more than 5 days in children under 12 years
- fever gets worse or lasts more than 3 days
- new symptoms occur
- redness or swelling is present

These could be signs of a serious condition.

PREGNANCY OR BREAST FEEDING

If pregnant or breast-feeding,ask a health professional before use.

Keep out of reach of children.

Overdose warning

Taking more than the recommended dose (overdose) may cause liver damage. In case of overdose, get medical help or contact a Poison Control Center right away. Quick medical attention is critical for adults as well as for children even if you do not notice any signs or symptoms.

Directions

Do not take more than directed
(see overdose warning)

Adults and children 12 years and over | - take 2 softgels every 4 to 6 hours while symptoms last - do not take more than 10 softgels in 24 hours - do not use for more than 10 days unless directed by a doctor
Children 6-11 years | - take 1 softgel every 4 to 6 hours while symptoms last - do not take more than 5 softgels 24 hours - do not use for more than 5 days unless directed by a doctorr
children under 6 years | - ask a doctor

Other information

- store at room temperature 15°-30°C (59°-86°F) and avoid excessive heat

Inactive ingredients

FD&C red #40, FD&C yellow #6, gelatin, glycerin, polyethylene glycol, povidone, propylene glycol, purified water, sorbitol special and white edible ink.

Manufactured by:
Humanwell PuraCap Pharmaceutical (Wuhan) Ltd.
Wuhan, Hubei
430206, China

PRINCIPAL DISPLAY PANEL - Shipping Label

ACETAMINOPHEN CAPSULES, 325 mg

Quantity : 5000 Capsules
NDC. No : 53345-010-01

IMPORTANT:

Inspect immediate upon receipt.
This is a bulk shipment intended for further processing only.
Protect from heat, humidity, and light. Do not refrigerate.

CAUTION : "FOR FURTHER MANUFACTURING, PROCESSING OR REPACKING"